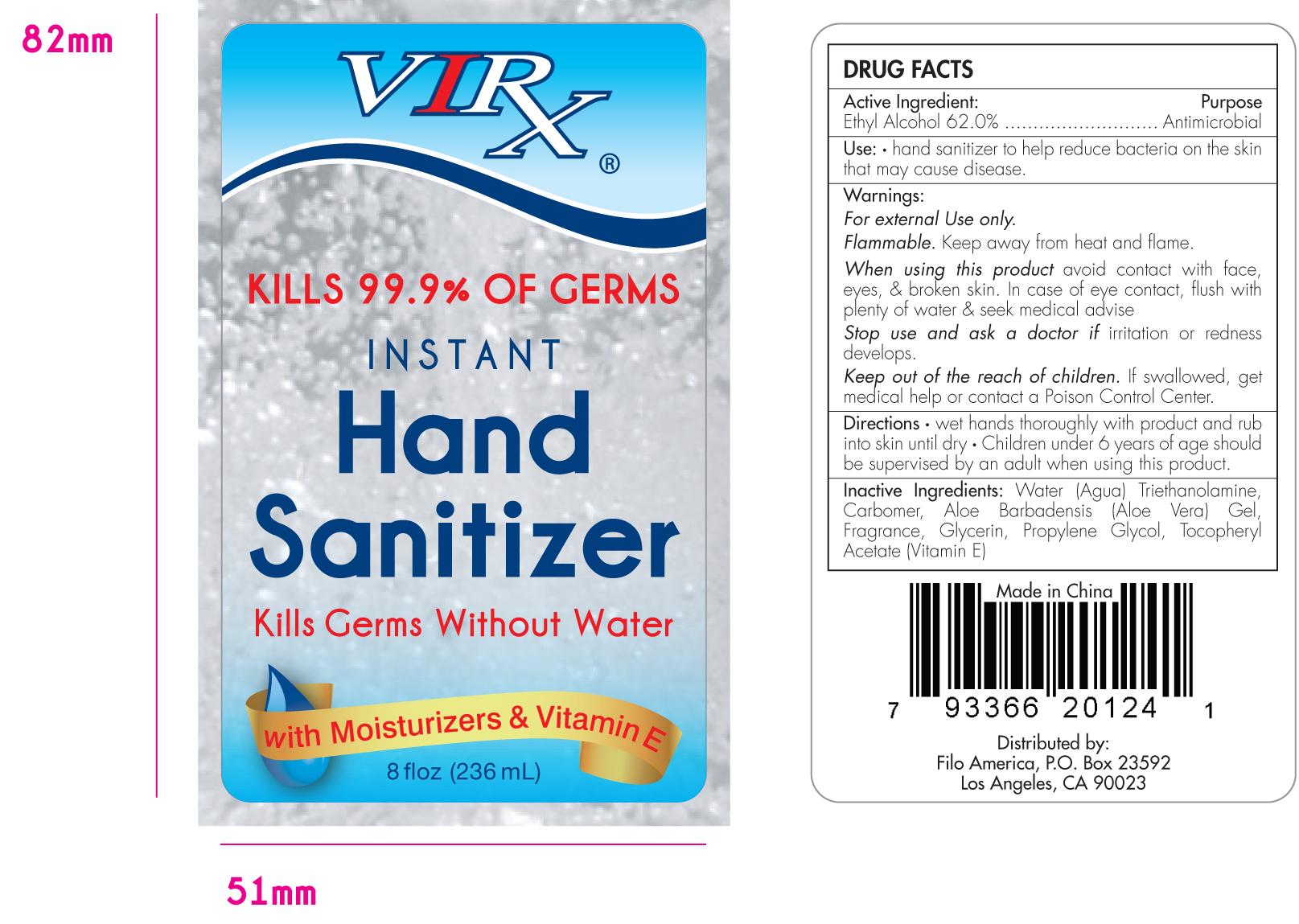 DRUG LABEL: Virx
NDC: 29860-205 | Form: GEL
Manufacturer: Ningbo United Group Co., Ltd.
Category: otc | Type: HUMAN OTC DRUG LABEL
Date: 20100302

ACTIVE INGREDIENTS: Alcohol 146.32 mL/236 mL
INACTIVE INGREDIENTS: Water; Trolamine; Carbomer 934; Aloe Vera Leaf; Glycerin; Propylene Glycol; ALPHA-TOCOPHEROL

Virx Instant Hand Sanitizer Drug Facts

ACTIVE INGREDIENT

Ethyl Alcohol 62.0%..................................Antimicrobial

WARNINGS

For external Use only.
Flammable. Keep away from heat and flame.

PURPOSE

Use hand sanitizer to help reduce bacteria on the skin that may cause disease.

When using this product avoid contact with face, eyes and broken skin. In case of eye contact, flush with plenty of water and seek medical advice.

Stop use and ask a doctor if irritation or redness develops.

KEEP OUT OF REACH OF CHILDREN

Keep out of the reach of children. If swallowed, get medical help or contact a Poison Control Center.

INDICATIONS AND USAGE

Directions wet hands thoroughly with product and rub into skin until dry. Children under 6 years of age should be supervised by an adult when using this product.

INACTIVE INGREDIENT

Water (Agua), Triethanolamine, Carbomer, Aloe Barbadensis (Aloe Vera) Gel, Fragrance, Glycerin, Propylene Glycol and Tocopheryl Acetate (Vitamin E).

PACKAGE LABEL

MM1